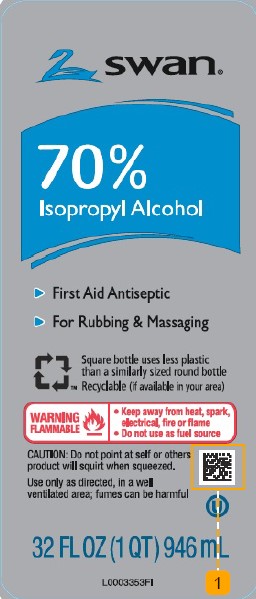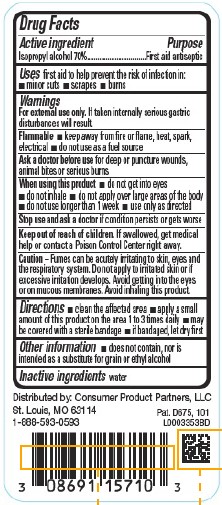 DRUG LABEL: Isopropyl Alcohol
NDC: 11344-810 | Form: LIQUID
Manufacturer: Consumer Product Partners, LLC
Category: otc | Type: HUMAN OTC DRUG LABEL
Date: 20250408

ACTIVE INGREDIENTS: ISOPROPYL ALCOHOL 70 mL/100 mL
INACTIVE INGREDIENTS: WATER

Swan 810.003/810AA
70% Isopropyl Alcohol

Active ingredient

Isopropyl alcohol 70%

Purpose

First aid antiseptic

Uses

first aid to help prevent the risk of infection in:

- minor cuts
- scrapes
- burns

Warnings

For external use only.If taken internally serious gastric disturbances will result.

Flammable

- Keep away from fire or flame, heat, spark, electrical
- do not use as a fuel source

Ask a doctor before use

for deep or puncutre wounds, animal bites or serious burns

When using this product

- do not get into eyes
- do not inhale
- do not apply over large areas of the body
- do not use longer than 1 week
- use only as directed

Stop use and ask a doctor if

if condition persists or gets worse

Keep out of reach of children.

If swallowed, get medical help or contact a Poison Control Center right away.

Caution

Fumes can be acutely irritating to skin, eyes and the respirtory system. Do not apply to irritated skin of if excessive irritation develops. Avoid getting into the eyes or on mucous membranes. Avoid inhaling this product

Directions

- clean the affected area
- apply a small amount of this product on the area 1 to 3 times daily
- may be covered with a sterile bandage
- if bandaged, let dry first

other information

- does not contain, nor is intended as a substitute for grain or ethyl alcohol

Inactive ingredient

water

Adverse reaction

Distributed by: Consumer Product Partners, LLC

St. Louis, MO 63114

1-888-593-0593

Pat. D675, 101

principal display panel

SWAN®

70% Isopropyl Alcohol

- First Aid Antseptic
- For Rubbing & Massaging

Square bottle uses less plastic than a similarly sized bottle

Recyclable (if available in your area)

WARNING FLAMMABLE

- Keep away from heat, spark, electrical fire or flame
- Do not use as fuel source

CAUTION: Do not point at self or other; product will squirt when squeezed.

Use only as directed, in a well-ventilated area: fumes can be harmful

32 FL OZ (1 QT) 946 mL